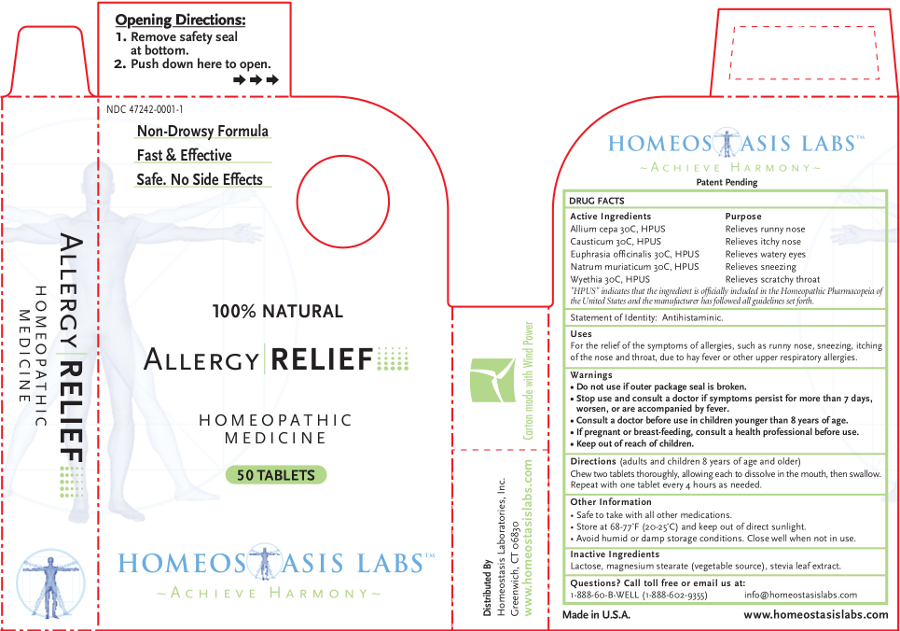 DRUG LABEL: Allergy RELIEF
NDC: 47242-0001 | Form: TABLET, CHEWABLE
Manufacturer: Homeostasis Laboratories, Inc.
Category: homeopathic | Type: HUMAN OTC DRUG LABEL
Date: 20121114

ACTIVE INGREDIENTS: ONION 30 [hp_C]/1 1; CAUSTICUM 30 [hp_C]/1 1; EUPHRASIA STRICTA 30 [hp_C]/1 1; SODIUM CHLORIDE 30 [hp_C]/1 1; WYETHIA HELENIOIDES ROOT 30 [hp_C]/1 1
INACTIVE INGREDIENTS: LACTOSE; MAGNESIUM STEARATE; STEVIA LEAF

Allergy RELIEF

Active Ingredients | Purpose
Allium cepa 30C, HPUS | Relieves runny nose
Causticum 30C, HPUS | Relieves itchy nose
Euphrasia officinalis 30C, HPUS | Relieves watery eyes
Natrum muriaticum 30C, HPUS | Relieves sneezing
Wyethia 30C, HPUS | Relieves scratchy throat

"HPUS" indicates that the ingredient is officially included in the Homeopathic Pharmacopeia of the United States and the manufacturer has followed all guidelines set forth.

Statement of Identity: Antihistaminic.

Uses

For the relief of the symptoms of allergies, such as runny nose, sneezing, itching of the nose and throat, due to hay fever or other upper respiratory allergies.

Warnings

- Do not use if outer package seal is broken.
- Stop use and consult a doctor if symptoms persist for more than 7 days, worsen, or are accompanied by fever.
- Consult a doctor before use in children younger than 8 years of age.

PREGNANCY OR BREAST FEEDING

- If pregnant or breast-feeding, consult a health professional before use.

- Keep out of reach of children.

Directions

(adults and children 8 years of age and older)

Chew two tablets thoroughly, allowing each to dissolve in the mouth, then swallow. Repeat with one tablet every 4 hours as needed.

Other information

- Safe to take with all other medications.
- Store at 68-77°F (20-25°C) and keep out of direct sunlight.
- Avoid humid or damp storage conditions. Close well when not in use.

Inactive Ingredients

Lactose, magnesium stearate (vegetable source), stevia leaf extract.

Questions? Call toll free or email us at:

1-888-60-B-WELL (1-888-602-9355)

info@homeostasislabs.com